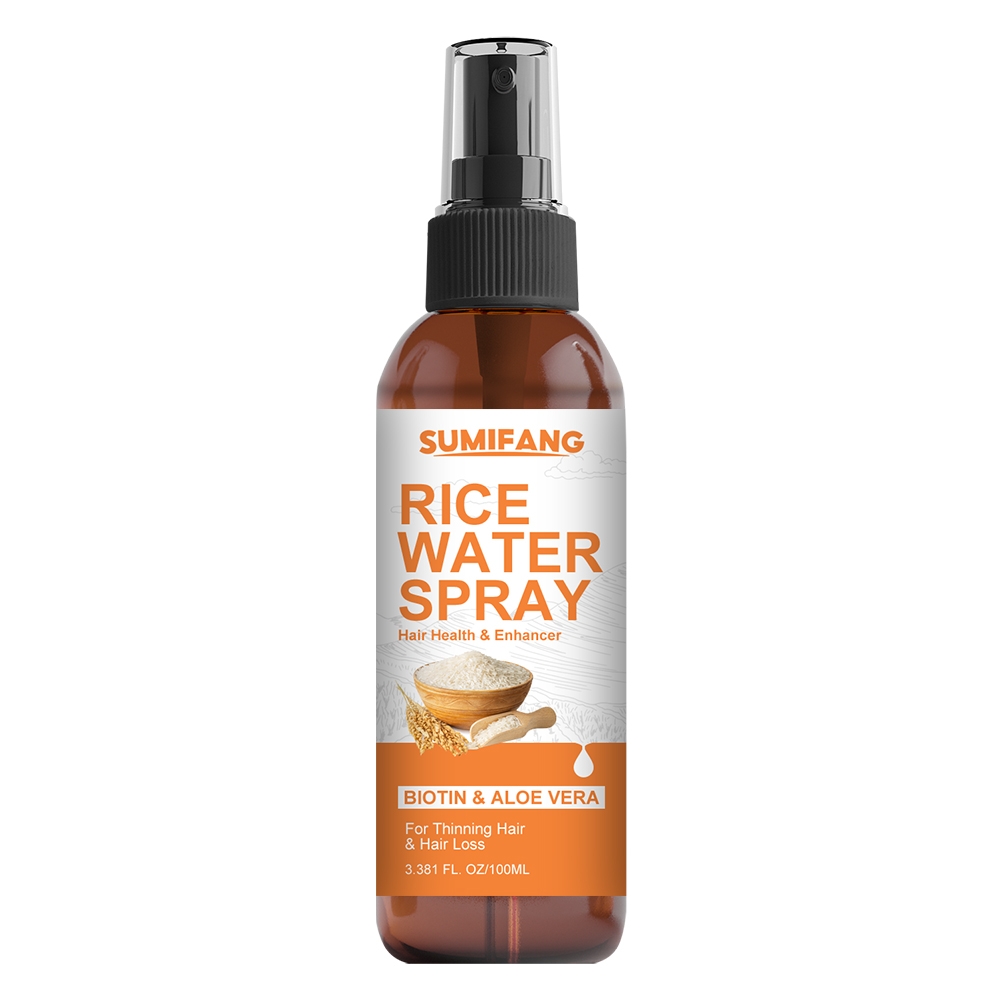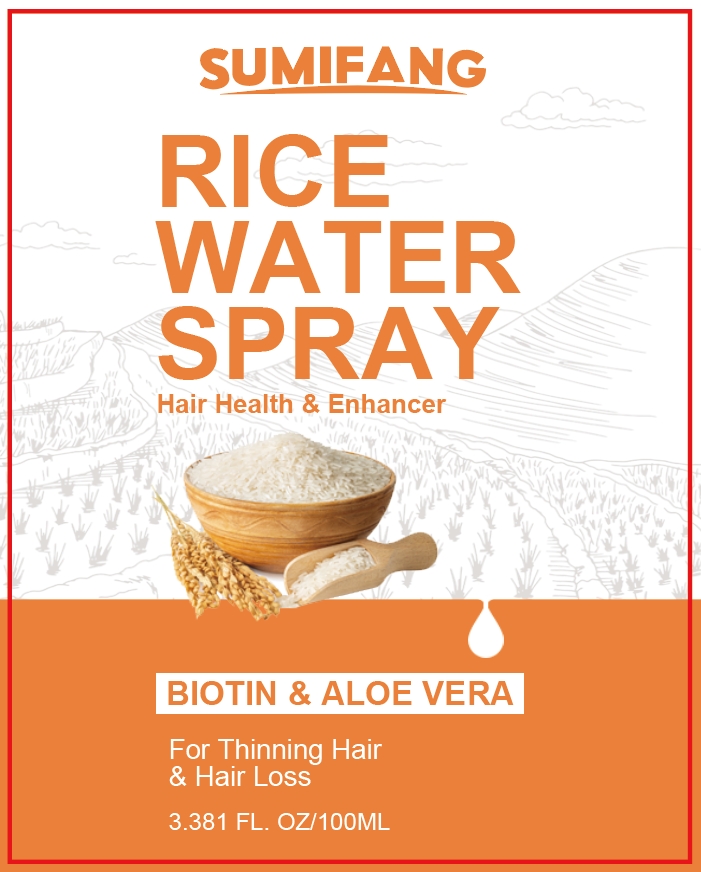 DRUG LABEL: RICE WATERSPRAY
NDC: 84025-143 | Form: SPRAY
Manufacturer: Guangzhou Yanxi Biotechnology Co.. Ltd
Category: otc | Type: HUMAN OTC DRUG LABEL
Date: 20240814

ACTIVE INGREDIENTS: ASCORBIC ACID 5 mg/100 mL; PANTHENOL 3 mg/100 mL
INACTIVE INGREDIENTS: WATER

DOSAGE AND ADMINISTRATION

Spray for treating hair loss and dry hair

WARNINGS

Keep out of children

INACTIVE INGREDIENT

Aqua

INDICATIONS AND USAGE

For daily hair care

Keep out of children

PURPOSE

Maintain and improve healthy hair growth